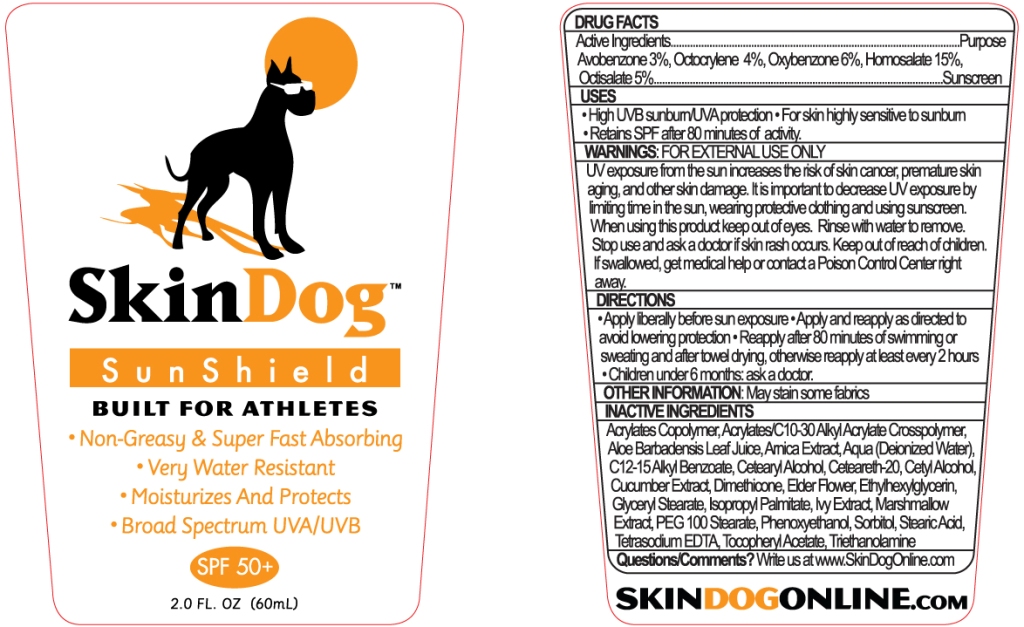 DRUG LABEL: SkinDog
NDC: 42657-111 | Form: LOTION
Manufacturer: SkinDog, LLC
Category: otc | Type: HUMAN OTC DRUG LABEL
Date: 20120105

ACTIVE INGREDIENTS: Avobenzone 1.70 g/56.7 g; Homosalate 8.5 g/56.7 g; Oxybenzone 3.4 g/56.7 g; Octisalate 2.8 g/56.7 g; Octocrylene 2.27 g/56.7 g
INACTIVE INGREDIENTS: Water; SORBITOL; Isopropyl Palmitate; C12-15 ALKYL BENZOATE; GLYCERYL DISTEARATE; STEARIC ACID; ALKYL (C12-15) BENZOATE; CETYL ALCOHOL; POLYOXYL 100 STEARATE; CARBOMER COPOLYMER TYPE A; ALOE VERA LEAF; Dimethicone; ALPHA-TOCOPHEROL ACETATE; CETOSTEARYL ALCOHOL; POLYOXYL 20 CETOSTEARYL ETHER; CUCUMBER; HEDERA HELIX LEAF; ALTHAEA OFFICINALIS ROOT; EDETATE SODIUM; TROLAMINE

Drug Facts

PACKAGE LABEL

Active Ingredients: Purpose
Avobenzone 3.0%...................................................................................................Sunscreen (A)
Octocrylene 4.0%...................................................................................................Sunscreen (B)
Oxybenzone 6.0%...................................................................................................Suncreeen (A)
Homosalate 15.0%.................................................................................................Sunscreen (B)
Octisalate 5.0%...................................................................................................Sunscreen (B)

Uses

- High UVB sunburn/UVA protection
- for skin highly sensitive to sunburn
- retains SPF after 80 minutes of activity

Warnings

For External use only
UV exposure from the sun increases the risk of skin cancer, premature skin aging, and other skin damage. It is important to decrease UV exposure by limiting time in the sun, wearing protective clothing, and using sunscreen.

Directions

- Apply liberally before sun exposure.
- Apply and reapply as directed to avoid lowering protection.
- Reapply after 80 minutes of swimming or sweating and after towel drying. Otherwise reapply at least every 2 hours.
- Children under 6 months; ask a doctor.

Inactive Ingredients

Aqua; Acrylates/C10-30 Alkyl Acrylate Crosspolymer; Sorbitol; Marshmellow Extract,; Ivy Extract; Cucumber Extract; Elder Flower; Arnica Extract; EDTA; Aloe Barbadensis Leaf Juice; Isopropyl Palmitate; Stearic Acid; PEG100 Stearate; Dimethicone; Cetyl Alcohol; Glyceryl Stearate; C12-15 Alkyl Benzoate; Cetearyl Alcohol, Ceteareth-20; Phenoxyethanol Ethylhexyl Glycerin; Triethanolamine; Tetrasodium EDTA; Tocopheryl Acetate

When using this product keep out of eyes.

Rinse with water to remove.
May stain some fabrics

Keep out of reach of children. If swallowed, get medical help or contact a Poison Control Center right away.

Stop use and ask a doctor if skin rash occurs.